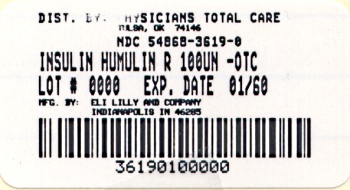 DRUG LABEL: Humulin R

                      
NDC: 54868-3619 | Form: INJECTION, SOLUTION
Manufacturer: Physicians Total Care, Inc.
Category: otc | Type: HUMAN OTC DRUG LABEL
Date: 20101108

ACTIVE INGREDIENTS: insulin human
 100 [iU]/1 mL
INACTIVE INGREDIENTS: glycerin 16 mg/1 mL; Metacresol 2.5 mg/1 mL; Water; Hydrochloric acid; Sodium hydroxide

HUMULIN® R
REGULAR
INSULIN HUMAN INJECTION, USP
(rDNA ORIGIN)100 UNITS PER ML (U-100)

INFORMATION FOR THE PHYSICIAN

HUMULIN® R
REGULAR
INSULIN HUMAN INJECTION, USP
(rDNA ORIGIN)
100 UNITS PER ML (U-100)

DESCRIPTION

Humulin® R U-100 is a polypeptide hormone structurally identical to human insulin synthesized through rDNA technology in a special non-disease-producing laboratory strain of Escherichia coli bacteria. Humulin R U-100 has the empirical formula C257H383N65O77S6 and a molecular weight of 5808.

Humulin R U-100 is a sterile, clear, aqueous, and colorless solution that contains human insulin (rDNA origin) 100 units/mL, glycerin 16 mg/mL and metacresol 2.5 mg/mL, endogenous zinc (approximately 0.015 mg/100 units) and water for injection. The pH is 7.0 to 7.8. Sodium hydroxide and/or hydrochloric acid may be added during manufacture to adjust the pH.

Adequate insulin dosage permits patients with diabetes to effectively utilize carbohydrates, proteins and fats. Regardless of dose strength, insulin enables carbohydrate metabolism to occur and thus to prevent the production of ketone bodies by the liver. Some patients develop severe insulin resistance such that daily doses of several hundred units of insulin or more are required.

CLINICAL PHARMACOLOGY

Regulation of glucose metabolism is the primary activity of insulin. Insulin lowers blood glucose by stimulating peripheral glucose uptake by skeletal muscle and fat, and by inhibiting hepatic glucose production. Insulins inhibit lipolysis, proteolysis, and gluconeogenesis, and enhance protein synthesis and conversion of excess glucose into fat.

Administered insulin, including Humulin R U-100, substitutes for inadequate endogenous insulin secretion and partially corrects the disordered metabolism and inappropriate hyperglycemia of diabetes mellitus, which are caused by either a deficiency or a reduction in the biologic effectiveness of insulin. When administered in appropriate doses at prescribed intervals to patients with diabetes mellitus, Humulin R U-100 restores their ability to metabolize carbohydrates, proteins and fats.

As with all insulin preparations, the duration of action of Humulin R U-100 is dependent on dose, site of injection, blood supply, temperature, and physical activity.

Humulin R U-100 is human insulin with a short duration of action. With subcutaneous use, the pharmacologic effect of Humulin R U-100 begins approximately 30 minutes (range: 10 to 75 minutes) after administration of doses in the 0.05 to 0.4 units/kg range. The effect is maximal at approximately 3 hours (range: 20 minutes to 7 hours) and terminates after approximately 8 hours (range: 3 to 14 hours). With intravenous use, the pharmacologic effect of Humulin R U-100 begins at approximately 10 to 15 minutes and terminates at a median time of approximately 4 hours (range: 2 to 6 hours) after administration of doses in the range of 0.1 to 0.2 units/kg. The time course of action of any insulin may vary considerably in different individuals or at different times in the same individual.

CLINICAL STUDIES

Subcutaneous use of Humulin R U-100

A 48-month multicenter, open-label, single-arm study was conducted in insulin-naive patients with type 1 or type 2 diabetes (N=129) to assess the safety and efficacy of Humulin R U-100. Humulin R U-100 and Humulin® N (alone or in combination) were administered by subcutaneous injection. Eighty-four percent of patients were Caucasian. Fifty-seven percent of the patients were male. The mean age was 45 years (range: 4 to 83 years). The average weight was 72 kg.

Total mean (± SD) glycohemoglobin improved from baseline to endpoint (baseline: 14.3 ± 3.1%, endpoint: 10.1 ± 2.8%). Hemoglobin A1c was not measured in this study. At baseline, patients weighed 72 ± 23 kg; at endpoint mean weight was 80 ± 22 kg. At endpoint, mean (± SD) total daily insulin doses for Humulin R U-100 were 0.18 ± 0.17 units/kg. At 48 months, 16 patients (21%) reported hypoglycemia. During the study, 4 patients experienced diabetic ketoacidosis.

Intravenous use of Humulin R U-100

The intravenous administration of Humulin R U-100 was tested in 21 patients with type 1 diabetes. The patients' usual doses of insulin were temporarily held, and blood glucose concentrations were maintained at a range of 200 – 260 mg/dL for one to three hours during a run-in phase of intravenous Humulin R U-100 followed by a 6-hour assessment phase. During the assessment phase patients received intravenous Humulin R at an initial dose of 0.5 U/h, adjusted to maintain blood glucose concentrations near normoglycemia (100 to 160 mg/dL).

The mean blood glucose levels during the assessment phase for patients on Humulin R U-100 therapy are summarized below in Table 1. All patients achieved near normoglycemia during the 6-hour assessment phase. At the endpoint, blood glucose was within the target range (100 to 160 mg/dL) for 20 of 21 patients treated with Humulin R U-100. The average time (± SE) required to attain near normoglycemia was 161 ± 14 minutes for Humulin R U-100.

Table 1: Mean Blood Glucose Concentrations (mg/dL) during Intravenous Infusions of Humulin R U-100
Time from Start of Infusion (min) | Mean Blood Glucose (mg/dL) Intravenousa
0 | 220 ± 11
30 | 204 ± 17
60 | 193 ± 18
120 | 172 ± 28
180 | 153 ± 30
240 | 139 ± 24
300 | 131 ± 22
360 | 128 ± 18
a Results shown as mean ± Standard Deviation.

INDICATIONS AND USAGE

Humulin R U-100 is indicated as an adjunct to diet and exercise to improve glycemic control in adults and children with type 1 and type 2 diabetes mellitus.

Humulin R U-100 may be administered intravenously under proper medical supervision in a clinical setting for glycemic control (see DOSAGE AND ADMINISTRATION and Storage).

CONTRAINDICATIONS

Humulin R U-100 is contraindicated during episodes of hypoglycemia and in patients hypersensitive to Humulin R U-100 or any of its excipients.

WARNINGS

Any change in insulin should be made cautiously and only under medical supervision. Changes in insulin strength, manufacturer, type (e.g., regular, NPH, analog, etc.), species, or method of administration may result in the need for a change in dosage.

PRECAUTIONS

Hypoglycemia

Hypoglycemia is the most common adverse reaction of all insulin therapies, including Humulin R U-100. Severe hypoglycemia may lead to unconsciousness and/or convulsions and may result in temporary or permanent impairment of brain function or death. Severe hypoglycemia requiring the assistance of another person and/or parenteral glucose infusion or glucagon administration has been observed in clinical trials with insulin, including trials with Humulin R U-100.

As with all insulin preparations, the time course of Humulin R U-100 action may vary in different individuals or at different times in the same individual and is dependent on dose, site of injection, blood supply, temperature, and physical activity.

Adjustment of dosage of any insulin may be necessary if patients change their physical activity or their usual meal plan. Insulin requirements may be altered during illness, emotional disturbances, or other stresses. Concomitant antihyperglycemic agents may need to be adjusted.

The timing of hypoglycemia usually reflects the time-action profile of the administered insulin formulations. Other factors such as changes in food intake (e.g., amount of food or timing of meals), injection site, exercise, and concomitant medications may also alter the risk of hypoglycemia (see PRECAUTIONS, Drug Interactions).

As with all insulins, use caution in patients with hypoglycemia unawareness and in patients who may be predisposed to hypoglycemia (e.g., the pediatric population and patients who fast or have erratic food intake). The patient's ability to concentrate and react may be impaired as a result of hypoglycemia. This may present a risk in situations where these abilities are especially important, such as driving or operating other machinery.

Hyperglycemia, Diabetic Ketoacidosis, and Hyperosmolar Non-Ketotic Syndrome

Hyperglycemia, diabetic ketoacidosis, or hyperosmolar coma may develop if the patient takes less Humulin R U-100 than needed to control blood glucose levels. This could be due to increases in insulin demand during illness or infection, neglect of diet, omission or improper administration of prescribed insulin doses or use of drugs that affect glucose metabolism or insulin sensitivity. Early signs of diabetic ketoacidosis include glycosuria and ketonuria. Polydipsia, polyuria, loss of appetite, fatigue, dry skin, abdominal pain, nausea and vomiting and compensatory tachypnea come on gradually, usually over a period of some hours or days, in conjunction with hyperglycemia and ketonemia. Severe sustained hyperglycemia may result in hyperosmolar coma or death.

Hypokalemia

Insulin stimulates potassium movement into the cells, possibly leading to hypokalemia, that left untreated may cause respiratory paralysis, ventricular arrhythmia, and death. Since intravenously administered insulin has a rapid onset of action, increased attention to hypokalemia is necessary. Therefore, potassium levels must be monitored closely when Humulin R U-100 or any other insulin is administered intravenously. Use caution in patients who may be at risk for hypokalemia (e.g., patients using potassium-lowering medications, patients taking medications sensitive to serum potassium concentrations).

Hypersensitivity and Allergic Reactions

Severe, life-threatening, generalized allergy, including anaphylaxis, can occur with insulin products, including Humulin R U-100 (see ADVERSE REACTIONS).

Localized reactions and generalized myalgias have been reported with the use of metacresol as an injectable excipient.

Renal or Hepatic Impairment

Frequent glucose monitoring and insulin dose reduction may be required in patients with renal or hepatic impairment.

Drug Interactions

Some medications may alter insulin requirements and the risk for hypoglycemia and hyperglycemia (see ADVERSE REACTIONS, Drug Interactions).

Use in Pregnancy

Pregnancy Category B. All pregnancies have a background risk of birth defects, miscarriage, or other adverse outcome regardless of drug exposure. This background risk is increased in pregnancies complicated by hyperglycemia and is decreased with good glucose control. It is important for patients to maintain good control of diabetes before conception and during pregnancy. Special attention should be paid to diet, exercise and insulin regimens. Insulin requirements may decrease during the first trimester, usually increase during the second and third trimesters, and rapidly decline after delivery. Careful monitoring is essential in these patients. Female patients should be advised to tell their physician if they intend to become, or if they become pregnant.

Studies show that endogenous insulin only crosses the placenta in minimal amounts. While there are no adequate and well-controlled studies in pregnant women, an extensive body of published literature demonstrates the maternal and fetal benefits of insulin treatment in patients with diabetes during pregnancy. Humulin R is a recombinant human insulin that is identical to the endogenous hormone; therefore, reproduction and fertility studies were not performed in animals.

Labor and Delivery

Careful glucose monitoring and management of patients with diabetes during labor and delivery are required.

Nursing Mothers

Endogenous insulin is present in human milk. Insulin orally ingested is degraded in the gastrointestinal tract. No adverse reactions have been associated with infant exposure to insulin through the consumption of human milk. In a study of eight preterm infants between 26 to 30 weeks gestation, enteral administration of Humulin R did not result in hypoglycemia. Good glucose control supports lactation in patients with diabetes. Patients with diabetes who are lactating may require adjustments in insulin dose and/or diet.

ADVERSE REACTIONS

Hypoglycemia

Hypoglycemia is one of the most frequent adverse events experienced by insulin users.

Symptoms of mild to moderate hypoglycemia may occur suddenly and can include:

- sweating

- drowsiness

- dizziness

- sleep disturbances

- palpitation

- anxiety

- tremor

- blurred vision

- hunger

- slurred speech

- restlessness

- depressed mood

- tingling in the hands, feet, lips, or tongue

- irritability

- lightheadedness

- abnormal behavior

- inability to concentrate

- unsteady movement

- headache

- personality changes

Signs of severe hypoglycemia can include:

- disorientation

- seizures

- unconsciousness

- coma

- death

Early warning symptoms of hypoglycemia may be different or less pronounced under certain conditions, such as long duration of diabetes, autonomic diabetic neuropathy, use of medications such as beta-adrenergic blockers, changing insulin preparations, or intensified control (3 or more insulin injections per day) of diabetes.

Without recognition of early warning symptoms, the patient may not be able to take steps to avoid more serious hypoglycemia. Patients who experience hypoglycemia without early warning symptoms should monitor their blood glucose more frequently, especially prior to activities such as driving. Mild to moderate hypoglycemia may be treated by eating foods or taking drinks that contain sugar. Patients should always carry a quick source of sugar, such as hard candy, non-diet carbohydrate-containing drinks or glucose tablets.

Hypokalemia

See Precautions

Lipodystrophy

Administration of insulin subcutaneously can result in lipoatrophy (depression in the skin) or lipohypertrophy (enlargement or thickening of tissue).

Allergy

Local Allergy – Patients occasionally experience erythema, local edema, and pruritus at the site of injection. This condition usually is self-limiting. In some instances, this condition may be related to factors other than insulin, such as irritants in the skin cleansing agent or poor injection technique.

Systemic Allergy – Less common, but potentially more serious, is generalized allergy to insulin, which may cause rash over the whole body, shortness of breath, wheezing, reduction in blood pressure, fast pulse, or sweating. Severe cases of generalized allergy (anaphylaxis) may be life threatening.

Weight Gain

Weight gain can occur with some insulin therapies and has been attributed to the anabolic effects of insulin and the decrease in glycosuria.

Peripheral Edema

Insulin may cause sodium retention and edema, particularly if previously poor metabolic control is improved by intensified insulin therapy.

Drug Interactions

A number of substances affect glucose metabolism and may require insulin dose adjustment and particularly close monitoring.

Drugs that may increase the blood-glucose-lowering effect of Humulin R U-100 and susceptibility to hypoglycemia:

- Oral antihyperglycemic agents, salicylates, sulfa antibiotics, certain antidepressants (monoamine oxidase inhibitors, selective serotonin reuptake inhibitors [SSRIs]), pramlintide, disopyramide, fibrates, fluoxetine, propoxyphene, pentoxifylline, ACE inhibitors, angiotensin II receptor blocking agents, beta-adrenergic blockers, inhibitors of pancreatic function (e.g., octreotide), and alcohol.

Drugs that may reduce the blood-glucose-lowering effect:

- Corticosteroids, isoniazid, certain lipid-lowering drugs (e.g., niacin), estrogens, oral contraceptives, phenothiazines, danazol, diuretics, sympathomimetic agents, somatropin, atypical antipsychotics, glucagon, protease inhibitors and thyroid replacement therapy.

Drugs that may increase or decrease blood-glucose-lowering effect:

- Beta-adrenergic blockers, clonidine, lithium salts, and alcohol.
- Pentamidine may cause hypoglycemia, which may sometimes be followed by hyperglycemia.

Drugs that may mask the signs of hypoglycemia:

- Beta-adrenergic blockers, clonidine, guanethidine, and reserpine.

OVERDOSAGE

Excess insulin may cause hypoglycemia and hypokalemia, particularly after intravenous administration. Hypoglycemia may occur as a result of an excess of insulin relative to food intake, energy expenditure, or both. Mild episodes of hypoglycemia usually can be treated with oral glucose. Adjustments in drug dosage, meal patterns, or exercise may be needed. More severe episodes with coma, seizure, or neurologic impairment may be treated with intramuscular/subcutaneous glucagon or concentrated intravenous glucose. Sustained carbohydrate intake and observation may be necessary because hypoglycemia may recur after apparent clinical recovery. Hypokalemia must be corrected appropriately.

DOSAGE AND ADMINISTRATION

Humulin R U-100, when used subcutaneously, is usually given three or more times daily before meals. The dosage and timing of Humulin R U-100 should be individualized and determined, based on the physician's advice, in accordance with the needs of the patient. Humulin R U-100 may also be used in combination with oral antihyperglycemic agents or longer-acting insulin products to suit the needs of the individual patients with diabetes. The injection of Humulin R U-100 should be followed by a meal within approximately 30 minutes of administration.

The average range of total daily insulin requirement for maintenance therapy in insulin-treated patients without severe insulin resistance lies between 0.5 and 1 unit/kg/day. However, in pre-pubertal children it usually varies from 0.7 to 1 unit/kg/day, but can be much lower during the period of partial remission. In situations of insulin resistance, e.g. during puberty or due to obesity, the daily insulin requirement may be substantially higher. Initial dosages for patients with diabetes are often lower, e.g., 0.2 to 0.4 units/kg/day.

Humulin R U-100 may be administered by subcutaneous injection in the abdominal wall, the thigh, the gluteal region or in the upper arm. Subcutaneous injection into the abdominal wall ensures a faster absorption than from other injection sites. Injection into a lifted skin fold minimizes the risk of intramuscular injection. Injection sites should be rotated within the same region. As with all insulin, the duration of action will vary according to the dose, injection site, blood flow, temperature, and level of physical activity.

Intravenous administration of Humulin R U-100 is possible under medical supervision with close monitoring of blood glucose and potassium levels to avoid hypoglycemia and hypokalemia.

For intravenous use, Humulin R U-100 should be used at concentrations from 0.1 unit/mL to 1 unit/mL in infusion systems with the infusion fluids 0.9% sodium chloride using polyvinyl chloride infusion bags.

Parenteral drug products should be inspected visually for particulate matter and discoloration prior to administration, whenever solution and container permit. Never use Humulin R U-100 if it has become viscous (thickened) or cloudy; use it only if it is clear and colorless. Humulin R U-100 should not be used after the printed expiration date.

Mixing of Insulins

- Humulin R U-100 should only be mixed as directed by the physician.
- Humulin R U-100 is short-acting and is often used in combination with intermediate- or long-acting insulins.
- The order of mixing and brand or model of syringe should be specified by the physician. A U-100 insulin syringe should always be used. Failure to use the correct syringe can lead to dosage errors.
- In general, when an intermediate-acting insulin (e.g., NPH insulin isophane suspension) is mixed with short-acting soluble insulin (e.g., regular), the short-acting insulin should be drawn into the syringe first.

Storage

Not in-use (unopened): Humulin R U-100 vials not in-use should be stored in a refrigerator (2° to 8°C [36° to 46°F]), but not in the freezer.

In-use (opened): The Humulin R U-100 vial currently in-use can be kept unrefrigerated as long as it is kept as cool as possible [below 30°C (86°F)] away from heat and light. In-use vials must be used within 31 days or be discarded, even if they still contain Humulin R U-100.

Admixture: Infusion bags prepared with Humulin R U-100 as indicated under DOSAGE AND ADMINISTRATION are stable when stored in a refrigerator (2° to 8°C [36° to 46°F]) for 48 hours and then may be used at room temperature for up to an additional 48 hours.

Do not use Humulin R U-100 after the expiration date stamped on the label or if it has been frozen.

HOW SUPPLIED

Humulin R U-100, Regular, insulin human injection, USP (rDNA origin), 100 units/mL, is supplied as follows:

10 mL vials NDC 54868-3619-0

Literature revised May 5, 2011

Marketed by: Lilly USA, LLC, Indianapolis, IN 46285, USA

www.lilly.com

Copyright © 2011, Eli Lilly and Company. All rights reserved.

PV 8261 AMP

Additional barcode label applied by:
Physicians Total Care, Inc.
Tulsa, Oklahoma 74146
Revised 12/12/2011

PATIENT INFORMATION

HUMULIN® R
REGULAR
INSULIN HUMAN INJECTION, USP
(rDNA ORIGIN)100 UNITS PER ML (U-100)

WARNINGS

THIS LILLY HUMAN INSULIN PRODUCT DIFFERS FROM ANIMAL-SOURCE INSULINS BECAUSE IT IS STRUCTURALLY IDENTICAL TO THE INSULIN PRODUCED BY YOUR BODY'S PANCREAS AND BECAUSE OF ITS UNIQUE MANUFACTURING PROCESS.

ANY CHANGE OF INSULIN SHOULD BE MADE CAUTIOUSLY AND ONLY UNDER MEDICAL SUPERVISION. CHANGES IN STRENGTH, MANUFACTURER, TYPE (E.G., REGULAR, NPH, ANALOG), SPECIES, OR METHOD OF MANUFACTURE MAY RESULT IN THE NEED FOR A CHANGE IN DOSAGE.

SOME PATIENTS TAKING HUMULIN® (HUMAN INSULIN, rDNA ORIGIN) MAY REQUIRE A CHANGE IN DOSAGE FROM THAT USED WITH OTHER INSULINS. IF AN ADJUSTMENT IS NEEDED, IT MAY OCCUR WITH THE FIRST DOSE OR DURING THE FIRST SEVERAL WEEKS OR MONTHS.

DIABETES

Insulin is a hormone produced by the pancreas, a large gland that lies near the stomach. This hormone is necessary for the body's correct use of food, especially sugar. Diabetes occurs when the pancreas does not make enough insulin to meet your body's needs.

To control your diabetes, your doctor has prescribed injections of insulin products to keep your blood glucose at a near-normal level. You have been instructed to test your blood regularly for glucose. Studies have shown that some chronic complications of diabetes such as eye disease, kidney disease, and nerve disease can be significantly reduced if the blood sugar is maintained as close to normal as possible. Proper control of your diabetes requires close and constant cooperation with your doctor. Despite diabetes, you can lead an active and healthy life if you eat a balanced diet, exercise regularly, and take your insulin injections as prescribed by your doctor.

Always keep an extra supply of insulin as well as a spare syringe and needle on hand. Always wear diabetic identification so that appropriate treatment can be given if complications occur away from home.

REGULAR HUMAN INSULIN

Description

Humulin is synthesized in a special non-disease-producing laboratory strain of Escherichia coli bacteria that has been genetically altered to produce human insulin. Humulin R [Regular insulin human injection, USP (rDNA origin)] consists of zinc-insulin crystals dissolved in a clear fluid. It takes effect within 30 minutes and has a duration of activity of approximately 4 to 12 hours. The time course of action of any insulin may vary considerably in different individuals or at different times in the same individual. As with all insulin preparations, the duration of action of Humulin R is dependent on dose, site of injection, blood supply, temperature, and physical activity. Humulin R is a sterile solution and is for subcutaneous injection. It should not be used intramuscularly. The concentration of Humulin R is 100 units/mL (U-100).

Identification

Human insulin from Eli Lilly and Company has the trademark Humulin. Your doctor has prescribed the type of insulin that he/she believes is best for you.

DO NOT USE ANY OTHER INSULIN EXCEPT ON YOUR DOCTOR'S ADVICE AND DIRECTION.

Always check the carton and the bottle label for the name and letter designation of the insulin you receive from your pharmacy to make sure it is the same as prescribed by your doctor. There are two Humulin R formulations: Humulin R U-100 and Humulin R U-500. Make sure that you have the formulation prescribed by your doctor.

Always check the appearance of your bottle of Humulin R before withdrawing each dose. Humulin R is a clear and colorless liquid with a water-like appearance and consistency. Do not use Humulin R:

- if it appears cloudy, thickened, or slightly colored, or
- if solid particles are visible.

If you see anything unusual in the appearance of Humulin R solution in your bottle or notice your insulin requirements changing, talk to your doctor.

Storage

Not in-use (unopened): Humulin R U-100 bottles not in-use should be stored in a refrigerator (36° to 46°F [2° to 8°C]), but not in the freezer.

In-use (opened): The Humulin R U-100 bottle you are currently using can be kept unrefrigerated as long as it is kept as cool as possible [below 86°F (30°C)] away from heat and light. In-use bottles must be used within 31 days or be thrown out, even if they still contain Humulin R U-100.

Do not use Humulin R after the expiration date stamped on the label or if it has been frozen.

DOSAGE

Your doctor has told you which insulin to use, how much, and when and how often to inject it. Because each patient's diabetes is different, this schedule has been individualized for you.

Your usual dose of Humulin R may be affected by changes in your diet, activity, or work schedule. Carefully follow your doctor's instructions to allow for these changes. Other things that may affect your Humulin R dose are:

Illness

Illness, especially with nausea and vomiting, may cause your insulin requirements to change. Even if you are not eating, you will still require insulin. You and your doctor should establish a sick day plan for you to use in case of illness. When you are sick, test your blood glucose frequently. If instructed by your doctor, test your ketones and report the results to your doctor.

Pregnancy

Good control of diabetes is especially important for you and your unborn baby. Pregnancy may make managing your diabetes more difficult. If you are planning to have a baby, are pregnant, or are nursing a baby, talk to your doctor.

Medication

Insulin requirements may be increased if you are taking other drugs with blood-glucose-raising activity, such as oral contraceptives, corticosteroids, or thyroid replacement therapy. Insulin requirements may be reduced in the presence of drugs that lower blood glucose or affect how your body responds to insulin, such as oral antidiabetic agents, salicylates (for example, aspirin), sulfa antibiotics, alcohol, certain antidepressants and some kidney and blood pressure medicines. Your Health Care Professional may be aware of other medications that may affect your diabetes control. Therefore, always discuss any medications you are taking with your doctor.

Exercise

Exercise may lower your body's need for insulin during and for some time after the physical activity. Exercise may also speed up the effect of an insulin dose, especially if the exercise involves the area of injection site (for example, the leg should not be used for injection just prior to running). Discuss with your doctor how you should adjust your insulin regimen to accommodate exercise.

Travel

When traveling across more than 2 time zones, you should talk to your doctor concerning adjustments in your insulin schedule.

COMMON PROBLEMS OF DIABETES

Hypoglycemia (Low Blood Sugar)

Hypoglycemia (too little glucose in the blood) is one of the most frequent adverse events experienced by insulin users. It can be brought about by:

1. Missing or delaying meals.
2. Taking too much insulin.
3. Exercising or working more than usual.
4. An infection or illness associated with diarrhea or vomiting.
5. A change in the body's need for insulin.
6. Diseases of the adrenal, pituitary, or thyroid gland, or progression of kidney or liver disease.
7. Interactions with certain drugs, such as oral antidiabetic agents, salicylates (for example, aspirin), sulfa antibiotics, certain antidepressants and some kidney and blood pressure medicines.
8. Consumption of alcoholic beverages.

Symptoms of mild to moderate hypoglycemia may occur suddenly and can include:

- sweating

- drowsiness

- dizziness

- sleep disturbances

- palpitation

- anxiety

- tremor

- blurred vision

- hunger

- slurred speech

- restlessness

- depressed mood

- tingling in the hands, feet, lips, or tongue

- irritability

- lightheadedness

- abnormal behavior

- inability to concentrate

- unsteady movement

- headache

- personality changes

Signs of severe hypoglycemia can include:

- disorientation

- seizures

- unconsciousness

- death

Therefore, it is important that assistance be obtained immediately.

Early warning symptoms of hypoglycemia may be different or less pronounced under certain conditions, such as long duration of diabetes, diabetic nerve disease, use of medications such as beta-blockers, changing insulin preparations, or intensified control (3 or more insulin injections per day) of diabetes.

A few patients who have experienced hypoglycemic reactions after transfer from animal-source insulin to human insulin have reported that the early warning symptoms of hypoglycemia were less pronounced or different from those experienced with their previous insulin.

Without recognition of early warning symptoms, you may not be able to take steps to avoid more serious hypoglycemia. Be alert for all of the various types of symptoms that may indicate hypoglycemia. Patients who experience hypoglycemia without early warning symptoms should monitor their blood glucose frequently, especially prior to activities such as driving. If the blood glucose is below your normal fasting glucose, you should consider eating or drinking sugar-containing foods to treat your hypoglycemia.

Mild to moderate hypoglycemia may be treated by eating foods or drinks that contain sugar. Patients should always carry a quick source of sugar, such as hard candy or glucose tablets. More severe hypoglycemia may require the assistance of another person. Patients who are unable to take sugar orally or who are unconscious require an injection of glucagon or should be treated with intravenous administration of glucose at a medical facility.

You should learn to recognize your own symptoms of hypoglycemia. If you are uncertain about these symptoms, you should monitor your blood glucose frequently to help you learn to recognize the symptoms that you experience with hypoglycemia.

If you have frequent episodes of hypoglycemia or experience difficulty in recognizing the symptoms, you should talk to your doctor to discuss possible changes in therapy, meal plans, and/or exercise programs to help you avoid hypoglycemia.

Hyperglycemia (High Blood Sugar) and Diabetic Ketoacidosis (DKA)

Hyperglycemia (too much glucose in the blood) may develop if your body has too little insulin. Hyperglycemia can be brought about by any of the following:

1. Omitting your insulin or taking less than your doctor has prescribed.
2. Eating significantly more than your meal plan suggests.
3. Developing a fever, infection, or other significant stressful situation.

In patients with type 1 or insulin-dependent diabetes, prolonged hyperglycemia can result in DKA (a life-threatening emergency). The first symptoms of DKA usually come on gradually, over a period of hours or days, and include a drowsy feeling, flushed face, thirst, loss of appetite, and fruity odor on the breath. With DKA, blood and urine tests show large amounts of glucose and ketones. Heavy breathing and a rapid pulse are more severe symptoms. If uncorrected, prolonged hyperglycemia or DKA can lead to nausea, vomiting, stomach pain, dehydration, loss of consciousness, or death. Therefore, it is important that you obtain medical assistance immediately.

Lipodystrophy

Rarely, administration of insulin subcutaneously can result in lipoatrophy (seen as an apparent depression of the skin) or lipohypertrophy (seen as a raised area of the skin). If you notice either of these conditions, talk to your doctor. A change in your injection technique may help alleviate the problem.

Allergy

Local Allergy — Patients occasionally experience redness, swelling, and itching at the site of injection. This condition, called local allergy, usually clears up in a few days to a few weeks. In some instances, this condition may be related to factors other than insulin, such as irritants in the skin cleansing agent or poor injection technique. If you have local reactions, talk to your doctor.

Systemic Allergy — Less common, but potentially more serious, is generalized allergy to insulin, which may cause rash over the whole body, shortness of breath, wheezing, reduction in blood pressure, fast pulse, or sweating. Severe cases of generalized allergy may be life threatening. If you think you are having a generalized allergic reaction to insulin, call your doctor immediately.

ADDITIONAL INFORMATION

Information about diabetes may be obtained from your diabetes educator.

Additional information about diabetes and Humulin can be obtained by calling The Lilly Answers Center at 1-800-LillyRx (1-800-545-5979) or by visiting www.LillyDiabetes.com.

Patient Information revised March 25, 2011

Marketed by: Lilly USA, LLC, Indianapolis, IN 46285, USA

Copyright © 1997, 2011, Eli Lilly and Company. All rights reserved.

PV 5694 AMP

INSTRUCTIONS FOR INSULIN VIAL USE

NEVER SHARE NEEDLES AND SYRINGES.

Correct Syringe Type

Doses of insulin are measured in units. U-100 insulin contains 100 units/mL (1 mL=1 cc). With Humulin R, it is important to use a syringe that is marked for U-100 insulin preparations. Failure to use the proper syringe can lead to a mistake in dosage, causing serious problems for you, such as a blood glucose level that is too low or too high.

Syringe Use

To help avoid contamination and possible infection, follow these instructions exactly.

Disposable syringes and needles should be used only once and then discarded by placing the used needle in a puncture-resistant disposable container. Properly dispose of the puncture-resistant container as directed by your Health Care Professional.

Preparing the Dose

1. Wash your hands.
2. Inspect the insulin. Humulin R solution should look clear and colorless. Do not use Humulin R if it appears cloudy, thickened, or slightly colored, or if you see particles in the solution. Do not use Humulin R if you notice anything unusual in its appearance.
3. If using a new Humulin R bottle, flip off the plastic protective cap, but do not remove the stopper. Wipe the top of the bottle with an alcohol swab.
4. If you are mixing insulins, refer to the “Mixing Humulin R with Longer-Acting Human Insulins” section below.
5. Draw an amount of air into the syringe that is equal to the Humulin R dose. Put the needle through rubber top of the Humulin R bottle and inject the air into the bottle.
6. Turn the Humulin R bottle and syringe upside down. Hold the bottle and syringe firmly in one hand.
7. Making sure the tip of the needle is in the Humulin R solution, withdraw the correct dose of Humulin R into the syringe.
8. Before removing the needle from the Humulin R bottle, check the syringe for air bubbles. If bubbles are present, hold the syringe straight up and tap its side until the bubbles float to the top. Push the bubbles out with the plunger and then withdraw the correct dose.
9. Remove the needle from the bottle and lay the syringe down so that the needle does not touch anything.
10. If you do not need to mix your Humulin R with a longer-acting insulin, go to the “Injection Instructions” section below and follow the directions.

Mixing Humulin R with Longer-Acting Human Insulins

1. Humulin R should be mixed with longer-acting human insulins only on the advice of your doctor.
2. Draw an amount of air into the syringe that is equal to the amount of longer-acting insulin you are taking. Insert the needle into the longer-acting insulin bottle and inject the air. Withdraw the needle.
3. Draw an amount of air into the syringe that is equal to the amount of Humulin R you are taking. Insert the needle into the Humulin R bottle and inject the air, but do not withdraw the needle.
4. Turn the Humulin R bottle and syringe upside down.
5. Making sure the tip of the needle is in the Humulin R solution, withdraw the correct dose of Humulin R into the syringe.
6. Before removing the needle from the Humulin R bottle, check the syringe for air bubbles. If bubbles are present, hold the syringe straight up and tap its side until the bubbles float to the top. Push the bubbles out with the plunger and then withdraw the correct dose.
7. Remove the syringe with the needle from the Humulin R bottle and insert it into the longer-acting insulin bottle. Turn the longer-acting insulin bottle and syringe upside down. Hold the bottle and syringe firmly in one hand and shake gently. Making sure the tip of the needle is in the longer-acting insulin, withdraw the correct dose of longer-acting insulin.
8. Remove the needle from the bottle and lay the syringe down so that the needle does not touch anything.
9. Follow the directions under “Injection Instructions” section below.

Follow your doctor's instructions on whether to mix your insulins ahead of time or just before giving your injection. It is important to be consistent in your method.

Syringes from different manufacturers may vary in the amount of space between the bottom line and the needle. Because of this, do not change:

- the sequence of mixing, or
- the model and brand of syringe or needle that your doctor has prescribed.

Injection Instructions

1. To avoid tissue damage, choose a site for each injection that is at least 1/2 inch from the previous injection site. The usual sites of injection are abdomen, thighs, and arms.
2. Cleanse the skin with alcohol where the injection is to be made.
3. With one hand, stabilize the skin by spreading it or pinching up a large area.
4. Insert the needle as instructed by your doctor.
5. Push the plunger in as far as it will go.
6. Pull the needle out and apply gentle pressure over the injection site for several seconds. Do not rub the area.
7. Place the used needle in a puncture-resistant disposable container and properly dispose of the puncture-resistant container as directed by your Health Care Professional.

Patient Instruction for Use revised March 25, 2011

Marketed by: Lilly USA, LLC, Indianapolis, IN 46285, USA

Copyright © 1997, 2011, Eli Lilly and Company. All rights reserved.

PV 8270 AMP

PACKAGE LABEL

PACKAGE CARTON – HUMULIN R U-100 Vial 10 mL 1ct

NDC 54868-3619-0

10 mL

100 units per mL

Humulin® R

REGULAR

insulin human injection, USP

(rDNA origin)

U-100

ACTIVE INGREDIENT

Enter section text here

PURPOSE

Enter section text here

KEEP OUT OF REACH OF CHILDREN

Enter section text here

INACTIVE INGREDIENT

Enter section text here